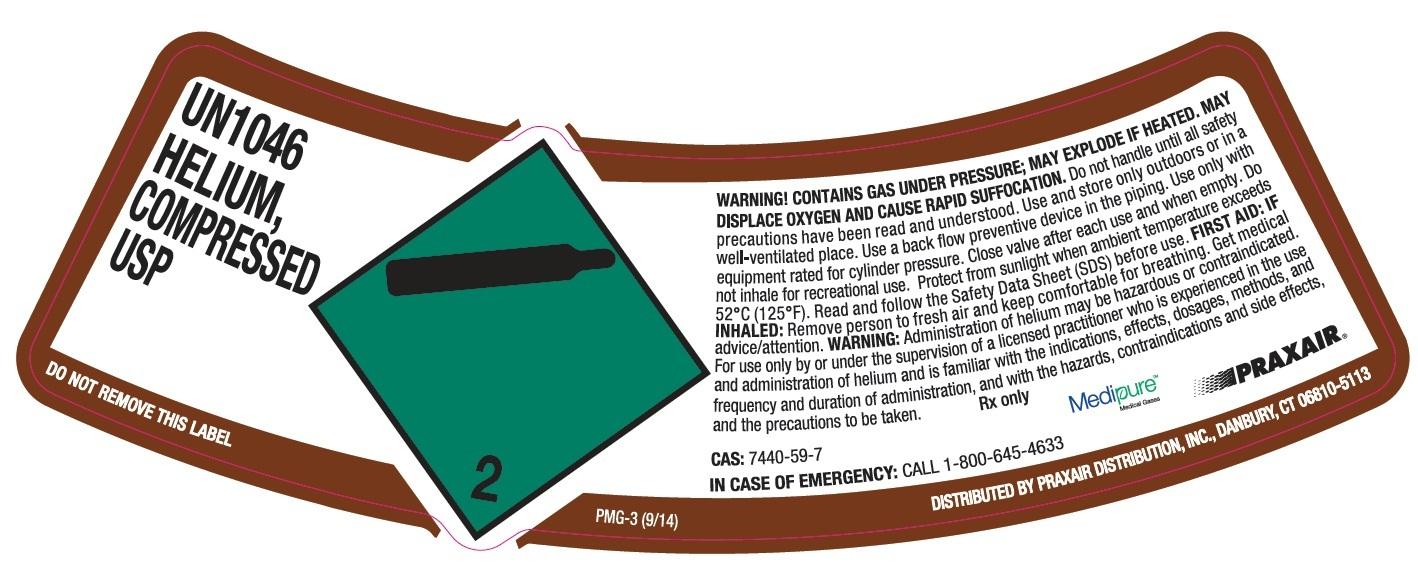 DRUG LABEL: Helium
NDC: 11324-005 | Form: GAS
Manufacturer: Praxair, Puerto Rico Inc.
Category: prescription | Type: HUMAN PRESCRIPTION DRUG LABEL
Date: 20221227

ACTIVE INGREDIENTS: HELIUM 990 mL/1 L

Helium USP Gurabo